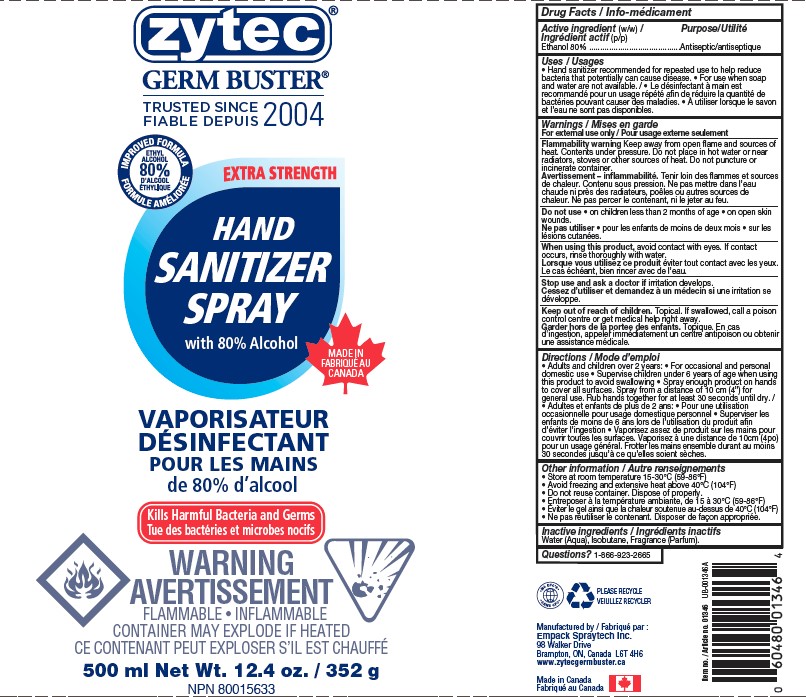 DRUG LABEL: Extra Stength Hand Sanitizer
NDC: 50021-008 | Form: AEROSOL, SPRAY
Manufacturer: Empack Spraytech Inc.
Category: otc | Type: HUMAN OTC DRUG LABEL
Date: 20241212

ACTIVE INGREDIENTS: ALCOHOL 80 g/100 g
INACTIVE INGREDIENTS: WATER; LIME (CITRUS); ISOBUTANE

50021-008 Extra Stength Hand Sanitizer

Active Ingredients (w/w)

Ethyl Alcohol 80%

Purpose

Antiseptic

Uses

Hand Sanitizer to help reduces bacteria that potentially can cause disease. Recommended for repeated use. For use when soap and

water are not available

Warnings

For external use only. Flammable. Keep away from fire or flame

Do not use

- in children less than 2 months age

- on open skin wounds

Stop use and ask a doctorif rash occurs.

WHEN USING

When using this productkeep out of eyes, ears, and mouth. in case of contact with eyes, rinse with water

Keep out of reach of children.If swallowed, get medical help or contact a Poison Control Center right away.

Directions

- Hold can at 10 inches distance
- Spray enough product on hands to cover all surfaces. Rub hands together until dry
- Supervise children under 6 years of age when using this product to avoid swallowing

Other Information

- Store at room temperature 15-30 C (59-86°F). May stain surfaces and fabrics.

- Avoid freezing and extrensive heat avbove 40C (104F)

Inactive Ingredients

Water (Aqua), Isobutane, Fragrance (Parfum).

Questions ?

1-866-923-2665

Manufactured in Canada by Empack Spraytech Inc., 98 Walker Drive, Brampton, ON, L6T 4H6

UPC Please recycle (+ logo) Lot # and Expiry Date to be embossed on the tube seal

Principal Display Panel -

Extra Stength Hand Sanitizer Spray

Alcohol Antiseptic 80%

Packge size ranges between 51g (100 ml) to 252g (500 ml)